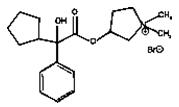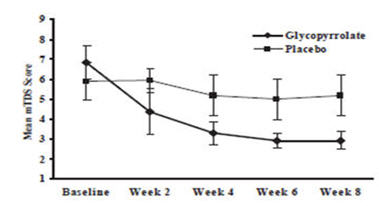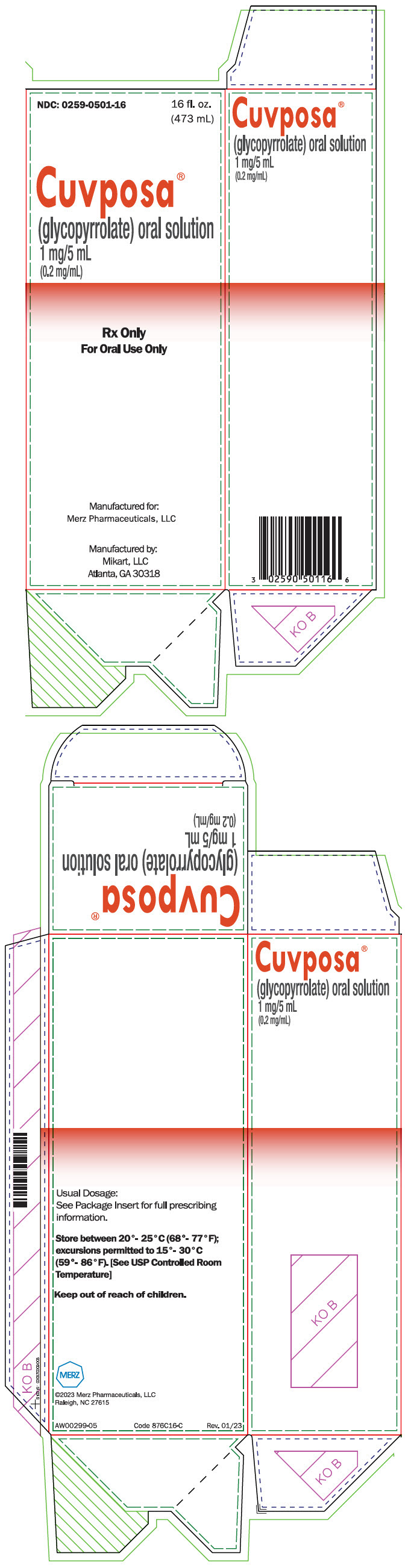 DRUG LABEL: Cuvposa
NDC: 0259-0501 | Form: LIQUID
Manufacturer: Merz Pharmaceuticals, LLC
Category: prescription | Type: HUMAN PRESCRIPTION DRUG LABEL
Date: 20241219

ACTIVE INGREDIENTS: GLYCOPYRROLATE 1 mg/5 mL
INACTIVE INGREDIENTS: SORBITOL; GLYCERIN; PROPYLENE GLYCOL; METHYLPARABEN; PROPYLPARABEN; CITRIC ACID MONOHYDRATE; SODIUM CITRATE, UNSPECIFIED FORM; SACCHARIN SODIUM; WATER

HIGHLIGHTS OF PRESCRIBING INFORMATION

These highlights do not include all the information needed to use CUVPOSA® safely and effectively. See full prescribing information for CUVPOSA.
CUVPOSA (glycopyrrolate) oral solution
Initial U.S. Approval: 1961

1 INDICATIONS AND USAGE

CUVPOSA is an anticholinergic indicated to reduce chronic severe drooling in patients aged 3-16 years with neurologic conditions associated with problem drooling (e.g., cerebral palsy). (1)

2 DOSAGE AND ADMINISTRATION

- Initiate dosing at 0.02 mg/kg three times daily and titrate in increments of 0.02 mg/kg every 5-7 days, based on therapeutic response and adverse reactions. (2)
- Maximum recommended dose is 0.1 mg/kg three times daily, not to exceed 1.5-3 mg per dose based upon weight. (2)
- Administer at least one hour before or two hours after meals. (2)

3 DOSAGE FORMS AND STRENGTHS

1 mg/5 mL, oral solution in 16 ounce bottles. (3)

4 CONTRAINDICATIONS

- Medical conditions that preclude anticholinergic therapy. (4)
- Concomitant use of solid oral dosage forms of potassium chloride. (4)

5 WARNINGS AND PRECAUTIONS

- Constipation or intestinal pseudo-obstruction: May present as abdominal distention, pain, nausea, or vomiting. Assess patients for constipation, particularly within 4-5 days of initial dosing or after a dose increase. (5.1)
- Incomplete mechanical intestinal obstruction: May present as diarrhea. If obstruction is suspected, discontinue CUVPOSA and evaluate. (5.2)
- High ambient temperature: To reduce the risk of heat prostration, avoid high temperatures. (5.3)

6 ADVERSE REACTIONS

The most common adverse reactions (incidence ≥30%) are dry mouth, vomiting, constipation, flushing, and nasal congestion. (6)

To report SUSPECTED ADVERSE REACTIONS, contact Merz Pharmaceuticals, LLC at 1-844-469-6379 or FDA at 1-800-FDA-1088 or www.fda.gov/medwatch.

7 DRUG INTERACTIONS

- Digoxin tablets: Use with glycopyrrolate can increase digoxin serum levels. Monitor patients and consider use of alternative dosage forms of digoxin. (7)
- Amantadine: Effects of glycopyrrolate may be increased with concomitant administration of amantadine. Consider decreasing the dose of glycopyrrolate during concomitant use. (7)
- Atenolol or metformin: Glycopyrrolate may increase serum levels of atenolol or metformin. Consider dose reduction when used with glycopyrrolate. (7)
- Haloperidol or levodopa: Glycopyrrolate may decrease serum levels of haloperidol or levodopa. Consider a dose increase when used with glycopyrrolate. (7)

8 USE IN SPECIFIC POPULATIONS

- Pediatric use: The safety and effectiveness of glycopyrrolate has not been established in patients less than 3 years of age. (8.4)
- Renal impairment: Use CUVPOSA with caution in patients with renal impairment. (8.6)

FULL PRESCRIBING INFORMATION

1 INDICATIONS AND USAGE

CUVPOSA is indicated to reduce chronic severe drooling in patients aged 3 to 16 years with neurologic conditions associated with problem drooling (e.g., cerebral palsy).

2 DOSAGE AND ADMINISTRATION

CUVPOSA must be measured and administered with an accurate measuring device [see Patient Counseling Information (17)].

Initiate dosing at 0.02 mg/kg orally three times daily and titrate in increments of 0.02 mg/kg every 5-7 days based on therapeutic response and adverse reactions. The maximum recommended dosage is 0.1 mg/kg three times daily not to exceed 1.5-3 mg per dose based upon weight. For greater detail, see Table 1.

During the four-week titration period, dosing can be increased with the recommended dose titration schedule while ensuring that the anticholinergic adverse events are tolerable. Prior to each increase in dose, review the tolerability of the current dose level with the patient's caregiver.

CUVPOSA should be dosed at least one hour before or two hours after meals.

The presence of high fat food reduces the oral bioavailability of CUVPOSA if taken shortly after a meal [see Clinical Pharmacology (12.3)].

Table 1: Recommended Dose Titration Schedule (each dose to be given three times daily)
Weight |  | Dose Level 1 |  | Dose Level 2 |  | Dose Level 3 |  | Dose Level 4 |  | Dose Level 5
kg | lbs | (~0.02 mg/kg) |  | (~0.04 mg/kg) |  | (~0.06 mg/kg) |  | (~0.08 mg/kg) |  | (~0.1 mg/kg)
13-17 | 27-38 | 0.3 mg | 1.5 mL | 0.6 mg | 3 mL | 0.9 mg | 4.5 mL | 1.2 mg | 6 mL | 1.5 mg | 7.5 mL
18-22 | 39-49 | 0.4 mg | 2 mL | 0.8 mL | 4 mL | 1.2 mg | 6 mL | 1.6 mg | 8 mL | 2.0 mg | 10 mL
23-27 | 50-60 | 0.5 mg | 2.5 mL | 1.0 mg | 5 mL | 1.5 mg | 7.5 mL | 2.0 mg | 10 mL | 2.5 mg | 12.5 mL
28-32 | 61-71 | 0.6 mg | 3 mL | 1.2 mg | 6 mL | 1.8 mg | 9 mL | 2.4 mg | 12 mL | 3.0 mg | 15 mL
33-37 | 72-82 | 0.7 mg | 3.5 mL | 1.4 mg | 7 mL | 2.1 mg | 10.5 mL | 2.8 mg | 14 mL | 3.0 mg | 15 mL
38-42 | 83-93 | 0.8 mg | 4 mL | 1.6 mg | 8 mL | 2.4 mg | 12 mL | 3.0 mg | 15 mL | 3.0 mg | 15 mL
43-47 | 94-104 | 0.9 mg | 4.5 mL | 1.8 mg | 9 mL | 2.7 mg | 13.5 mL | 3.0 mg | 15 mL | 3.0 mg | 15 mL
≥48 | ≥105 | 1.0 mg | 5 mL | 2.0 mg | 10 mL | 3.0 mg | 15 mL | 3.0 mg | 15 mL | 3.0 mg | 15 mL

3 DOSAGE FORMS AND STRENGTHS

CUVPOSA is available as a 1mg/5 mL clear, cherry-flavored solution for oral administration in 16 ounce bottles.

4 CONTRAINDICATIONS

CUVPOSA is contraindicated in:

- Patients with medical conditions that preclude anticholinergic therapy (e.g., glaucoma, paralytic ileus, unstable cardiovascular status in acute hemorrhage, severe ulcerative colitis, toxic megacolon complicating ulcerative colitis, myasthenia gravis).
- Patients taking solid oral dosage forms of potassium chloride. The passage of potassium chloride tablets through the gastrointestinal (GI) tract may be arrested or delayed with coadministration of CUVPOSA.

5 WARNINGS AND PRECAUTIONS

5.1 Constipation or Intestinal Pseudo-obstruction

Constipation is a common dose-limiting adverse reaction which sometimes leads to glycopyrrolate discontinuation [see Adverse Reactions (6.1)]. Assess patients for constipation, particularly within 4-5 days of initial dosing or after a dose increase. Intestinal pseudo-obstruction has been reported and may present as abdominal distention, pain, nausea or vomiting.

5.2 Incomplete Mechanical Intestinal Obstruction

Diarrhea may be an early symptom of incomplete mechanical intestinal obstruction, especially in patients with ileostomy or colostomy. If incomplete mechanical intestinal obstruction is suspected, discontinue treatment with CUVPOSA and evaluate for intestinal obstruction.

5.3 High Ambient Temperatures

In the presence of high ambient temperature, heat prostration (fever and heat stroke due to decreased sweating) can occur with the use of anticholinergic drugs such as CUVPOSA. Advise patients/caregivers to avoid exposure of the patient to hot or very warm environmental temperatures.

5.4 Operating Machinery or an Automobile

CUVPOSA may produce drowsiness or blurred vision. As appropriate for a given age, warn the patient not to engage in activities requiring mental alertness such as operating a motor vehicle or other machinery, or performing hazardous work while taking CUVPOSA.

5.5 Anticholinergic Drug Effects

Use CUVPOSA with caution in patients with conditions that are exacerbated by anticholinergic drug effects including:

- Autonomic neuropathy
- Renal disease
- Ulcerative colitis – Large doses may suppress intestinal motility to the point of producing a paralytic ileus and for this reason may precipitate or aggravate "toxic megacolon", a serious complication of the disease
- Hyperthyroidism
- Coronary heart disease, congestive heart failure, cardiac tachyarrhythmias, tachycardia, and hypertension
- Hiatal hernia associated with reflux esophagitis, since anticholinergic drugs may aggravate this condition

6 ADVERSE REACTIONS

The following serious adverse reactions are described elsewhere in the labeling:

- Constipation or intestinal pseudo-obstruction [see Warnings and Precautions (5.1)]
- Incomplete mechanical intestinal obstruction [see Warnings and Precautions (5.2)]

The most common adverse reactions reported with CUVPOSA are dry mouth, vomiting, constipation, flushing, and nasal congestion.

6.1 Clinical Trials Experience

Because clinical trials are conducted under widely varying conditions, adverse reaction rates observed in the clinical trials of a drug cannot be directly compared to rates in the clinical trials of another drug and may not reflect the rates observed in practice.

The data described below reflect exposure to CUVPOSA in 151 subjects, including 20 subjects who participated in an 8-week placebo-controlled study (Study 1) and 137 subjects who participated in a 24-week open-label study (six subjects who received CUVPOSA in the placebo-controlled study and 131 new subjects).

Table 2 presents adverse reactions reported by ≥ 15% of CUVPOSA-treated subjects from the placebo-controlled clinical trial.

Table 2: Adverse Reactions Occurring in ≥ 15% of CUVPOSA-Treated Subjects and at a Greater Frequency than Placebo in Study 1
 | CUVPOSA (N=20) n (%) | Placebo (N=18) n (%)
Dry Mouth | 8 (40%) | 2 (11%)
Vomiting | 8 (40%) | 2 (11%)
Constipation | 7 (35%) | 4 (22%)
Flushing | 6 (30%) | 3 (17%)
Nasal Congestion | 6 (30%) | 2 (11%)
Headache | 3 (15%) | 1 (6%)
Sinusitis | 3 (15%) | 1 (6%)
Upper Respiratory Tract Infection | 3 (15%) | 0
Urinary Retention | 3 (15%) | 0

The following adverse reactions occurred at a rate of <2% of patients receiving CUVPOSA in the open-label study.

Gastrointestinal: Abdominal distention, abdominal pain, stomach discomfort, chapped lips, flatulence, retching, dry tongue
General Disorders: Irritability, pain
Infections: Pneumonia, sinusitis, tracheostomy infection, upper respiratory tract infection, urinary tract infection
Investigations: Heart rate increase
Metabolism and Nutrition: Dehydration
Nervous System: Headache, convulsion, dysgeusia, nystagmus
Psychiatric: Agitation, restlessness, abnormal behavior, aggression, crying, impulse control disorder, moaning, mood altered
Respiratory: Increased viscosity of bronchial secretion, nasal congestion, nasal dryness
Skin: Dry skin, pruritus, rash
Vascular: Pallor

6.2 Postmarketing Experience

The following adverse reactions have been identified during postapproval use of other formulations of glycopyrrolate for other indications. Because these reactions are reported voluntarily from a population of uncertain size, it is not always possible to reliably estimate their frequency or establish a causal relationship to drug exposure.

Additional adverse reactions identified during postapproval use of glycopyrrolate tablets include: loss of taste and suppression of lactation.

7 DRUG INTERACTIONS

Drugs Affected by Reduced GI Transit Time

Glycopyrrolate reduces GI transit time, which may result in altered release of certain drugs when formulated in delayed- or controlled-release dosage forms.

- The passage of potassium chloride tablets through the GI tract may be arrested or delayed with coadministration of glycopyrrolate. Solid dosage forms of potassium chloride are contraindicated [see Contraindications (4)].
- Digoxin administered as slow dissolution oral tablets may have increased serum levels and enhanced action when administered with glycopyrrolate. Monitor patients receiving slow dissolution digoxin for increased action if glycopyrrolate is coadministered regularly. Consider the use of other oral dosage forms of digoxin (e.g., elixir or capsules).

Amantadine

The anticholinergic effects of glycopyrrolate may be increased with concomitant administration of amantadine. Consider decreasing the dose of glycopyrrolate during coadministration of amantadine.

Drugs Whose Plasma Levels May be Increased by Glycopyrrolate

Coadministration of glycopyrrolate may result in increased levels of certain drugs.

- Atenolol's bioavailability may be increased with coadministration of glycopyrrolate. A reduction in the atenolol dose may be needed.
- Metformin plasma levels may be elevated with coadministration of glycopyrrolate, increasing metformin's pharmacologic and toxic effects. Monitor clinical response to metformin with concomitant glycopyrrolate administration; consider a dose reduction of metformin if warranted.

Drugs Whose Plasma Levels May be Decreased by Glycopyrrolate

Coadministration of glycopyrrolate may result in decreased levels of certain drugs.

- Haloperidol's serum level may be decreased when coadministered with glycopyrrolate, resulting in worsening of schizophrenic symptoms, and development of tardive dyskinesia. Closely monitor patients if coadministration cannot be avoided.
- Levodopa's therapeutic effect may be reduced with glycopyrrolate administration. Consider increasing the dose of levodopa.

8 USE IN SPECIFIC POPULATIONS

8.1 Pregnancy

Risk Summary

There are no available data in pregnant women for Cuvposa to inform decisions concerning any drug-associated risks. In pregnant rats, daily oral administration of glycopyrrolate during organogenesis at dose exposures 2.5 to 113 times the exposure at the maximum recommended human dose (MRHD) did not result in an increased incidence of gross external or visceral defects [see Data]. When glycopyrrolate was administered intravenously to pregnant rabbits during organogenesis at dose exposures equivalent to up to approximately 7.8 times the exposure at the MRHD, no adverse effects on embryo-fetal development were seen. The estimated background risk of major birth defects and miscarriage for the indicated population is unknown. In the U.S. general population, the estimated background risk of major birth defects and miscarriage in clinically recognized pregnancies is 2-4% and 15-20%, respectively.

Animal Data

Glycopyrrolate was orally administered to pregnant rats at dosages of 50, 200, and 400 mg/kg/day during the period of organogenesis. These dosages resulted in systemic exposures (estimated AUC0-inf values) approximately 2.5, 23, and 113 times, respectively, the estimated systemic exposure in humans at the MRHD (9 mg per day, administered in three divided doses). Glycopyrrolate had no effect on maternal survival, but significantly reduced mean maternal body weight gain over the period of dosing at all dosages evaluated. Mean fetal weight was significantly reduced in the 200 and 400 mg/kg/day dose groups. There were two litters with all resorbed fetuses in the 400 mg/kg/day dose group. There were no effects of treatment on the incidence of gross external or visceral defects. Minor treatment-related skeletal effects included reduced ossification of various bones in the 200 and 400 mg/kg/day dose groups; these skeletal effects were likely secondary to maternal toxicity.

Glycopyrrolate was intravenously administered to pregnant rabbits at dosages of 0.1, 0.5, and 1.0 mg/kg/day during the period of organogenesis. These dosages resulted in systemic exposures (estimated AUC0-inf values) approximately 0.8, 4.6, and 7.8 times, respectively, the estimated systemic exposure in humans at the MRHD. Glycopyrrolate did not affect maternal survival under the conditions of this study. Mean maternal body weight gain and mean food consumption over the period of dosing were lower than the corresponding control value in the 0.5 and 1.0 mg/kg/day treatment groups. There were no effects of treatment on fetal parameters, including fetal survival, mean fetal weight, and the incidence of external, visceral, or skeletal defects.

Female rats that were pregnant or nursing were orally dosed with glycopyrrolate daily at dosages of 0, 50, 200, or 400 mg/kg/day, beginning on day 7 of gestation, and continuing until day 20 of lactation. These dosages resulted in systemic exposures (estimated AUC0-inf values) approximately 2.5, 23, and 113 times, respectively, the estimated systemic exposure in humans at the MRHD (9 mg per day, administered in three divided doses). Mean body weight of pups in all treatment groups was reduced compared to the control group during the period of nursing, but eventually recovered to be comparable to the control group, post-weaning. No other notable delivery or litter parameters were affected by treatment in any group, including no effects on mean duration of gestation or mean numbers of live pups per litter. No treatment-related effects on survival or adverse clinical signs were observed in pups. There were no effects of maternal treatment on behavior, learning, memory, or reproductive function of pups.

8.2 Lactation

Risk Summary

There are no data on the presence of glycopyrrolate or its metabolites in human milk, the effects on the breastfed infant, or the effects on milk production. The developmental and health benefits of breastfeeding should be considered along with the mother's clinical need for CUVPOSA and any potential adverse effects on the breastfed infant from CUVPOSA or from the underlying maternal condition.

8.4 Pediatric Use

CUVPOSA was evaluated for chronic severe drooling in patients aged 3-16 years with neurologic conditions associated with problem drooling. CUVPOSA has not been studied in subjects under the age of 3 years.

8.5 Geriatric Use

Clinical studies of CUVPOSA did not include subjects aged 65 and over.

8.6 Renal Impairment

Because glycopyrrolate is largely renally eliminated, CUVPOSA should be used with caution in patients with renal impairment [see Clinical Pharmacology (12.3)].

10 OVERDOSAGE

Because glycopyrrolate is a quaternary amine which does not easily cross the blood-brain barrier, symptoms of glycopyrrolate overdosage are generally more peripheral in nature rather than central compared to other anticholinergic agents. In case of accidental overdose, therapy may include:

- Maintain an open airway, providing ventilation as necessary.
- Managing any acute conditions such as hyperthermia, coma and or seizures as applicable, and managing any jerky myoclonic movements or choreoathetosis which may lead to rhabdomyolysis in some cases of anticholinergic overdosage.
- Administering a quaternary ammonium anticholinesterase such as neostigmine to help alleviate-peripheral anticholinergic effects such as anticholinergic induced ileus.
- Administering activated charcoal orally as appropriate.

11 DESCRIPTION

CUVPOSA is an anticholinergic drug available as an oral solution containing 1 mg glycopyrrolate per 5 mL. The chemical name for glycopyrrolate is pyrrolidinium, 3-[(cyclopentylhydroxyphenylacetyl) oxy]-1,1-dimethyl-,bromide. The chemical structure is:

The empirical formula for CUVPOSA is C19H28BrNO3 and the molecular weight is 398.33. The inactive ingredients in CUVPOSA are: citric acid, glycerin, natural and artificial cherry flavor, methylparaben, propylene glycol, propylparaben, saccharin sodium, sodium citrate, sorbitol solution, and purified water.

12 CLINICAL PHARMACOLOGY

12.1 Mechanism of Action

Glycopyrrolate is a competitive inhibitor of acetylcholine receptors that are located on certain peripheral tissues, including salivary glands. Glycopyrrolate indirectly reduces the rate of salivation by preventing the stimulation of these receptors.

12.2 Pharmacodynamics

Glycopyrrolate inhibits the action of acetylcholine on salivary glands thereby reducing the extent of salivation.

12.3 Pharmacokinetics

Absorption

In a parallel study of children (n=6 per group) aged 7-14 years undergoing intraocular surgery, subjects received either intravenous (IV) or oral glycopyrrolate as a premedication. The mean absolute bioavailability of oral glycopyrrolate tablets was low (approximately 3%) and highly variable among subjects (range 1.3 to 13.3%). A similar pattern of low and variable relative bioavailability is seen in adults.

Analysis of population pharmacokinetic data from normal adults and children with cerebral palsy associated chronic moderate to severe drooling failed to demonstrate linear pharmacokinetics across the dose range. In the same analysis, population estimates of the apparent oral clearance (scaled by weight in children and adults) ranged from 5.28 - 38.95 L/hr/kg for healthy adults and 8.07 - 25.65 L/hr/kg for patients with cerebral palsy, a reflection of the low and highly variable oral bioavailability of glycopyrrolate.

Absorption of CUVPOSA (fasting) was compared to that of a marketed glycopyrrolate oral tablet. The Cmax after oral solution administration was 23% lower compared to tablet administration and AUC0-inf was 28% lower after oral solution administration. Mean Cmax after oral solution administration in the fasting state was 0.318 ng/mL, and mean AUC0-24 was 1.74 ng∙hr/mL. Mean time to maximum plasma concentration for CUVPOSA was 3.1 hours, and mean plasma half-life was 3.0 hours.

In healthy adults, a high fat meal was shown to significantly affect the absorption of glycopyrrolate oral solution (10 mL, 1 mg/5 mL). The mean Cmax under fed high fat meal conditions was approximately 74% lower than the Cmax observed under fasting conditions. Similarly, mean AUC0-T was reduced by about 78% by the high fat meal compared with the fasting AUC0-T. A high fat meal markedly reduces the oral bioavailability of CUVPOSA. Therefore, CUVPOSA should be dosed at least one hour before or two hours after meals. Pharmacokinetic results (mean ± SD) are described in Table 3.

Table 3: Pharmacokinetic Parameters (mean±SD) for CUVPOSA, Fasting and Fed, in Healthy Adults
 | Cmax (ng/mL) | Tmax (hrs) | AUC0-T (ng∙hr/mL) | AUC0-Inf (ng∙hr/mL) | T1/2 (hrs)
Fasting (n=37) | 0.318 ± 0.190 | 3.10 ± 1.08 | 1.74 ± 1.07 | 1.81 ± 1.09 | 3.0 ± 1.2
Fed (n=36) | 0.084 ± 0.081 | 2.60 ± 1.12 | 0.38 ± 0.14 | 0.46 ± 0.13 [n=35] | 3.2 ± 1.1

Distribution

After IV administration, glycopyrrolate has a mean volume of distribution in children aged 1 to 14 years of approximately 1.3 to 1.8 L/kg, with a range from 0.7 to 3.9 L/kg. In adults aged 60-75 years, the volume of distribution was lower (0.42 L/kg +/- 0.22).

Metabolism

In adult patients who underwent surgery for cholelithiasis and were given a single IV dose of tritiated glycopyrrolate, approximately 85% of total radioactivity was excreted in urine and <5% was present in T-tube drainage of bile. In both urine and bile, >80% of the radioactivity corresponded to unchanged drug. These data suggest a small proportion of IV glycopyrrolate is excreted as one or more metabolites.

Elimination

Approximately 65-80% of an IV glycopyrrolate dose was eliminated unchanged in urine in adults. In two studies, after IV administration to pediatric patients ages 1-14 years, mean clearance values ranged from 1.01- 1.41 L/kg/hr (range 0.32 -2.22 L/kg/hr). In adults, IV clearance values were 0.54 ± 0.14 L/kg/hr.

Pediatrics

The estimated apparent clearance of glycopyrrolate from a population pharmacokinetic analysis (scaled by weight in children and adults) of oral and IV data was found to be 13.2 L/hr/kg or 92.7 L/hr for a typical 70 kg subject. In the same population based analysis, gender was not identified as having an effect on either glycopyrrolate clearance or systemic exposure.

Gender

Population pharmacokinetic evaluation of adults and children administered IV or oral glycopyrrolate identified no effect of gender on glycopyrrolate clearance or systemic exposure.

Race

The pharmacokinetics of glycopyrrolate by race has not been characterized.

Elderly

Glycopyrrolate pharmacokinetics have not been characterized in the elderly.

Renal Impairment

In one study, glycopyrrolate 4 mcg/kg was administered intravenously in uremic patients undergoing renal transplantation surgery. Mean AUC (10.6 mcg∙h/L), mean plasma clearance (0.43 L/hr/kg) and mean 3-hour urinary excretion (0.7%) for glycopyrrolate were significantly different than those of control patients (3.73 µg∙h/L, 1.14 L/hr/kg, and 50%, respectively). These results suggest that elimination of glycopyrrolate is severely impaired in patients with renal failure.

Hepatic Impairment

Glycopyrrolate is largely renally eliminated. The pharmacokinetics of glycopyrrolate have not been evaluated in patients with hepatic impairment.

13 NONCLINICAL TOXICOLOGY

13.1 Carcinogenesis, Mutagenesis, Impairment of Fertility

When glycopyrrolate was administered via oral gavage to mice for up to 24 months at dosages of 2.5, 7, and 20 mg/kg/day in both genders, resulting in systemic exposures (estimated AUC0-inf values) approximately 0.1, 0.3, and 0.8 times, respectively, the estimated systemic exposure in humans at the MRHD (9 mg per day, administered in three divided doses), no significant changes in tumor incidence were observed when compared to control.

When glycopyrrolate was administered via oral gavage to rats for up to 24 months at dosages of 5, 15, and 40 mg/kg/day in both genders, resulting in systemic exposures approximately 0.2, 0.8, and 2 times, respectively, the estimated systemic exposure in humans at the MRHD, no significant changes in tumor incidence were observed when compared to control.

Glycopyrrolate did not elicit any genotoxic effects in the Ames mutagenicity assay, the human lymphocyte chromosome aberration assay, or the micronucleus assay.

Glycopyrrolate was assessed for effects on fertility or general reproductive function in rats. Rats of both genders received glycopyrrolate at dosages up to 100 mg/kg/day via oral gavage, resulting in systemic exposures (estimated AUC0-inf values) in males and females up to approximately 11 and 15 times, respectively, the estimated systemic exposure in humans at the MRHD. No treatment-related effects on fertility or reproductive parameters were observed in either gender in this study.

14 CLINICAL STUDIES

CUVPOSA was evaluated in a multi-center, randomized, double-blind, placebo-controlled, parallel, eight-week study for the control of pathologic drooling in children (Study 1). The study enrolled 38 subjects aged 3-23 years; thirty-six subjects were aged 3-16 years and two patients were greater than 16 years. The subjects were male or female, weighed at least 13 kg (27 lbs), and had cerebral palsy, mental retardation, or another neurologic condition associated with problem drooling defined as drooling in the absence of treatment so that clothing became damp on most days (approximately five to seven days per week). Subjects were randomized in a 1:1 fashion to receive CUVPOSA or placebo. Doses of study medication were titrated over a 4-week period to optimal response beginning at 0.02 mg/kg three times a day increasing doses in increments of approximately 0.02 mg/kg three times per day every 5-7 days, not to exceed the lesser of approximately 0.1 mg/kg three times per day or 3 mg three times per day.

Subjects were evaluated on the 9-point modified Teacher's Drooling Scale (mTDS), which is presented below. The mTDS evaluations were recorded by parents/caregivers 3 times daily approximately two hours post-dose on evaluation days during pre-treatment baseline and at Weeks 2, 4, 6 and 8 of therapy.

Modified Teacher's Drooling Scale

1= Dry: never drools
2= Mild: only the lips are wet; occasionally
3= Mild: only the lips are wet; frequently
4= Moderate: wet on the lips and chin; occasionally
5= Moderate: wet on the lips and chin; frequently
6= Severe: drools to the extent that clothing becomes damp; occasionally
7= Severe: drools to the extent that clothing becomes damp; frequently
8= Profuse: clothing, hands, tray, and objects become wet; occasionally
9= Profuse: clothing, hands, tray, and objects become wet; frequently

Responders were defined as subjects with at least a 3-point reduction in mean daily mTDS scores from baseline to Week 8. Table 4 presents the proportion of responders at Week 8 and Figure 1 presents the mean mTDS values from baseline through Week 8.

Table 4: Percentage of Responders at Week 8
CUVPOSA Group (N=20) | Placebo Group (N=18)
15/20 (75%) | 2/18 (11%)

Figure 1. Mean (± 2 Standard Errors) mDTS Scores

16 HOW SUPPLIED/STORAGE AND HANDLING

NDC 0259-0501-16; 1 mg/5mL clear, cherry-flavored solution; 16 oz. bottle.

STORAGE AND HANDLING

Store at room temperature 20° - 25°C (68° - 77°F); excursions permitted to 15° - 30°C (59° - 86°F) [See USP Controlled Room Temperature].

17 PATIENT COUNSELING INFORMATION

See FDA-approved patient labeling (Patient Information)

- Advise patients/caregivers to measure CUVPOSA with an accurate measuring device. A household teaspoon is not an accurate measuring device. Patients/caregivers should use a dosing cup available in pharmacies to accurately measure the correct milliliter dose. An oral syringe, also available in pharmacies, should be used to dispense CUVPOSA into the child's mouth from the cup. A pharmacist can recommend an appropriate measuring device and can provide instructions for measuring the correct dose.
- Administering CUVPOSA with a high fat meal substantially reduces the amount of glycopyrrolate absorbed. Administer CUVPOSA at least one hour before or two hours after meals.
- CUVPOSA is started at a low dose and gradually titrated over a period of weeks based on therapeutic response and adverse reactions. Patients/caregivers should not increase the dose without the physician's permission.
- Common adverse reactions from CUVPOSA include overly dry mouth, constipation, vomiting, flushing of the skin or face, and urinary retention. Side effects can sometimes be difficult to detect in some patients with neurologic problems who cannot adequately communicate how they feel. If side effects become troublesome after increasing a dose, decrease the dose to the prior one and contact your physician.
- Constipation is the most common side effect of glycopyrrolate, and if constipation occurs, stop administering glycopyrrolate to the patient and call their healthcare practitioner.
- Inability of the patient to urinate, dry diapers or undergarments, irritability or crying may be signs of urinary retention, and if urinary retention occurs, patients/caregivers should stop administering glycopyrrolate and call their healthcare practitioner.
- If the patient develops a skin rash, hives or an allergic reaction, patients/caregivers should stop administering glycopyrrolate and call their healthcare practitioner as this could be a sign of hypersensitivity to this product.
- Drugs like glycopyrrolate can reduce sweating, and if the patient is in a hot environment and flushing of the skin occurs this may be due to overheating. Avoid exposure of the patient to hot or very warm environmental temperatures to avoid overheating and the possibility of heat exhaustion or heat stroke.

Manufactured by:
Mikart, LLC
Atlanta, GA 30318

Manufactured for:
Merz Pharmaceuticals, LLC
Raleigh, NC 27615

© 2023 Merz Pharmaceuticals, LLC
CUVPOSA® is a registered trademark of Merz Pharmaceuticals, LLC

IN00187-01

PATIENT and CAREGIVER INFORMATION

CUVPOSA (glycopyrrolate) Oral Solution

Please read the Patient and Caregiver Information that comes with CUVPOSA before you start giving it to your child, and each time you get a refill. This leaflet does not take the place of talking with your doctor about your child's medical condition or treatment.

What is CUVPOSA?

CUVPOSA is a prescription medicine used in children with medical conditions that cause too much (abnormal) drooling.

Who should not take CUVPOSA?

Do not give CUVPOSA to anyone who:

- has problems urinating
- has a bowel problem called paralytic ileus
- lacks normal bowel tone or tension
- has severe ulcerative colitis or certain other serious bowel problems with severe ulcerative colitis
- has myasthenia gravis

What should I tell my doctor before giving CUVPOSA to my child?

Tell your doctor if your child:

- has any allergies
- has any stomach or bowel problems, including ulcerative colitis
- has any problems with constipation
- has thyroid problems
- has high blood pressure
- has heart problems or abnormal heart beats
- has a hiatal hernia with gastroesophageal reflux disease (GERD)
- has any eye problems
- has any problems urinating
- has any other medical conditions
- is pregnant or plans to become pregnant. It is not known if CUVPOSA can harm an unborn baby.
- is breastfeeding or plans to breastfeed. It is not known if CUVPOSA passes into breast milk and if it can harm the baby.

Tell your doctor about all of the medicines that your child takes, including prescription and non-prescription medicines, vitamins, and herbal supplements. Some medicine may affect the way CUVPOSA works, and CUVPOSA may affect how some other medicines work.

How should I give CUVPOSA?

- Give CUVPOSA exactly as prescribed by your child's doctor.
- Give CUVPOSA 1 hour before or 2 hours after meals.
- Your doctor will tell you how much (milliliters or mLs) of CUVPOSA to give your child.
- Do not change the dose of CUVPOSA unless your doctor tells you to.
- You must measure the dose of CUVPOSA before giving it to your child. Use a special marked dose measuring cup (available at most pharmacies) to measure the right dose of CUVPOSA.
- To help make sure that your child swallows the dose, you should use an oral syringe to give the child each dose of CUVPOSA, after you measure the dose needed with a dose measuring cup. Oral syringes are also available at most pharmacies.
- If you have questions about how to measure the dose or how to use an oral syringe, ask your pharmacist or doctor.
- The dose of CUVPOSA that is needed to control drooling may be different for each child. CUVPOSA is usually started at a low dose, and slowly increased as directed by your doctor. This slow increase in dose continues until the best dose for your child is reached, to control drooling.
- During this time it is important to stay in close contact with your child's doctor, and tell the doctor about any side effects that your child has. See "What are the possible side effects of CUVPOSA?"

What should I avoid while taking CUVPOSA?

- CUVPOSA may cause sleepiness or blurred vision. Do not drive a car, operate heavy machinery, or do other dangerous activities while taking CUVPOSA.
- Avoid overheating. See "What are the possible side effects of CUVPOSA?"

What are the possible side effects of CUVPOSA?

CUVPOSA can cause serious side effects including:

- Constipation. Constipation is common with CUVPOSA. Tell your doctor if your child strains with bowel movements, goes longer between bowel movements, cannot have a bowel movement, or their stomach is firm and large. The dose of CUVPOSA may need to be decreased or stopped.
- Diarrhea and intestinal blockage. Diarrhea can be an early symptom of a blockage in the intestine. This is especially true if your child has a colostomy or ileostomy. Tell your doctor if your child has any diarrhea while taking CUVPOSA.
- Problems with control of body temperature (overheating or heat stroke). CUVPOSA can cause your child to sweat less. Your child can become overheated, and develop heat stroke if they are in an area that is very hot. Avoid overheating. Call your doctor right away if your child becomes sick and has any of these symptoms of heatstroke:
  - hot, red skin
  - decreased alertness or passing out (unconsciousness)
  - fast, weak pulse
  - fast, shallow breathing
  - increased body temperature (fever)

The most common side effects of CUVPOSA include:

- dry mouth
- vomiting
- flushing of the face or skin
- nasal congestion
- headache
- swollen sinuses (sinusitis)
- upper respiratory tract infection
- problems urinating, difficulty starting urination

Tell your doctor if your child has any side effect that concerns you or that does not go away. These are not all the possible side effects of CUVPOSA.

Call your doctor for medical advice about side effects. You may report side effects to FDA at 1-800-FDA-1088.

How should I store CUVPOSA?

Store CUVPOSA between 68°F to 77°F (20°C to 25°C).

Keep CUVPOSA out of the reach of children.

General information about CUVPOSA:

Medicines are sometimes prescribed for purposes other than those listed in a Patient Information leaflet. Do not use CUVPOSA for a condition for which it was not prescribed. Do not give CUVPOSA to other people even if they have the same condition. It may harm them.

This leaflet summarizes the most important information about CUVPOSA. If you would like more information, talk with your doctor. You can ask your doctor or pharmacist for information about CUVPOSA that is written for health professionals.

For more information, go to: www.cuvposa.com or call 1-844-469-6379.

What are the ingredients in CUVPOSA?

Active Ingredient: glycopyrrolate

Inactive Ingredients: citric acid, glycerin, natural and artificial cherry flavor, methylparaben, propylene glycol, propylparaben, saccharin sodium, sodium citrate, sorbitol solution, and purified water

Issued May 2011

Manufactured by:
Mikart, LLC
Atlanta, GA 30318

Manufactured for:
Merz Pharmaceuticals, LLC
Raleigh, NC 27615

© 2023 Merz Pharmaceuticals, LLC
CUVPOSA® is a registered trademark of Merz Pharmaceuticals, LLC

IN00187-01
Rev 01/2023

PRINCIPAL DISPLAY PANEL - 473 mL Bottle Carton

NDC: 0259-0501-16

16 fl. oz.
(473 mL)

Cuvposa®
(glycopyrrolate) oral solution
1 mg/5 mL
(0.2 mg/mL)

Rx Only
For Oral Use Only

Manufactured for:
Merz Pharmaceuticals, LLC

Manufactured by:
Mikart, LLC
Atlanta, GA 30318